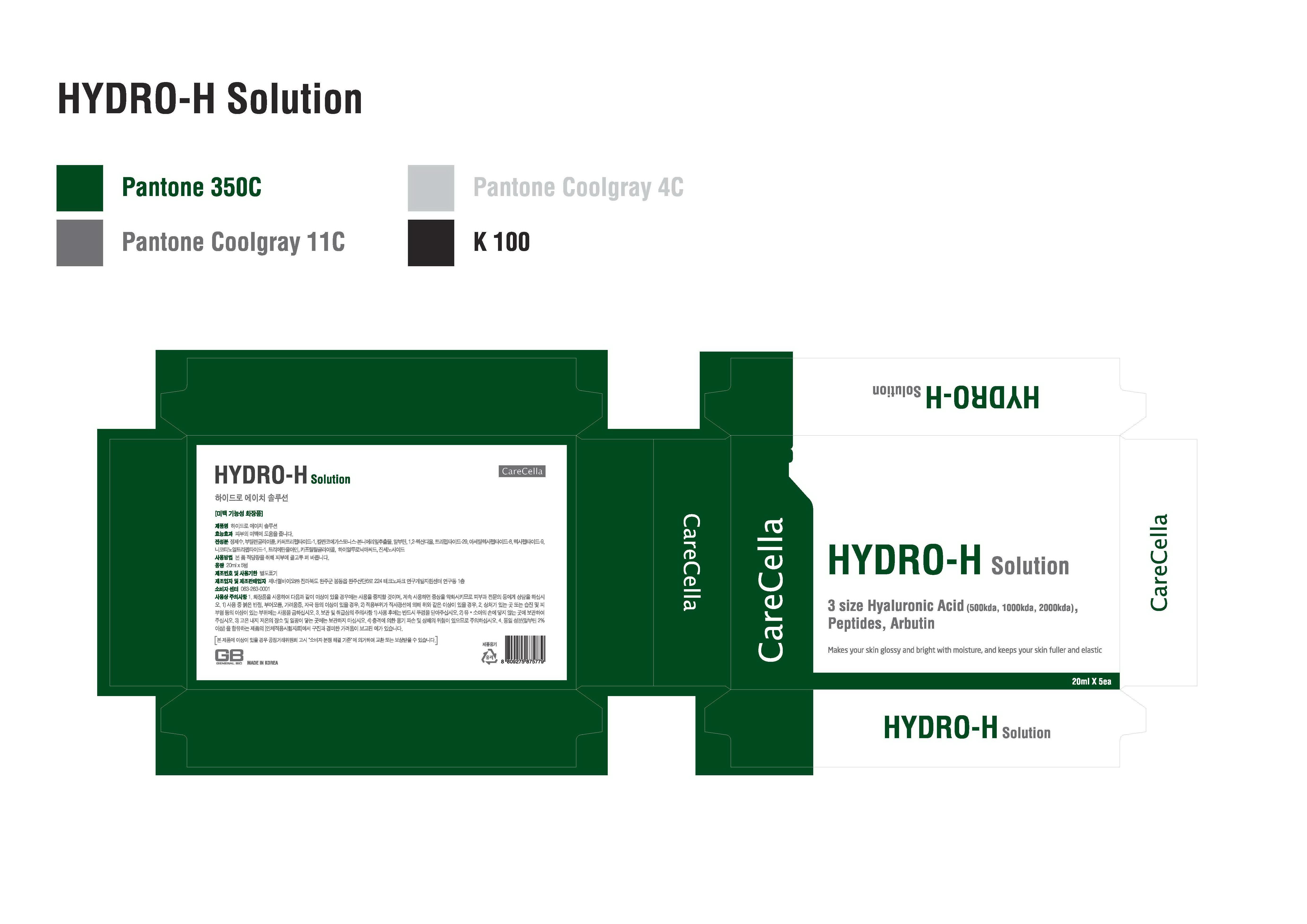 DRUG LABEL: HYDRO H
NDC: 69422-5001 | Form: SOLUTION
Manufacturer: General Bio Co., Ltd.
Category: otc | Type: HUMAN OTC DRUG LABEL
Date: 20141209

ACTIVE INGREDIENTS: ARBUTIN 2.5 mg/1 mL
INACTIVE INGREDIENTS: WATER; HYALURONIC ACID; PREZATIDE COPPER

Drug Facts

ACTIVE INGREDIENT

arbutin

INACTIVE INGREDIENT

water, hyaluronic acid,copper tripeptide-1, tripeptide-29, ginsenosides, etc

PURPOSE

skin whitening
skin protectant

keep out of reach of the children

INDICATIONS AND USAGE

apply proper amount to the skin

WARNINGS

・Stop using the product when you have skin problems or the product disagrees with your skin
・Stop using the product immediately and consult a dermatologist if you have redness, swelling, itching or irritation on the skin while or after using the product.
・If the product gets into the eyes, don't rub but rinse with water.
・Don't place the product in any place where it will be subjected to extremely high or low temperatures or direct sunlight.

DOSAGE AND ADMINISTRATION

for external use only